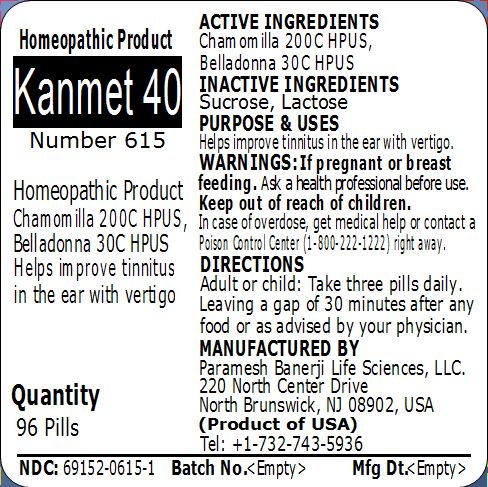 DRUG LABEL: Kanmet 40 (Number 615)
NDC: 69152-0615 | Form: PELLET
Manufacturer: Paramesh Banerji Life Sciences LLC
Category: homeopathic | Type: HUMAN OTC DRUG LABEL
Date: 20150309

ACTIVE INGREDIENTS: MATRICARIA RECUTITA 200 [hp_C]/1 1; ATROPA BELLADONNA 30 [hp_C]/1 1
INACTIVE INGREDIENTS: LACTOSE; SUCROSE

Active Ingredients

Chamomilla 200C HPUS, Belladonna 30C HPUS

Inactive Ingredients

Sucrose, Lactose

Purpose

Helps improve tinnitus in the ear with vertigo

Uses

Helps improve tinnitus in the ear with vertigo

Warnings

If pregnant or breast feeding ask a health professional before use.

Keep out of reach of children. In case of overdose, get medical help or contact a Poison Control Center (1-800-222-1222) right away.

Direction

Adult or child: Take three pills daily. Leaving a gap of 30 minutes after any food or as advised by your physician.

Manufactured by

Paramesh Banerji Life Sciences, LLC

220 North Center Drive

North Brunswick, NJ 08902, USA

Product of USA

Tel: +1-732-743-5936

Principal Display Panel

Homeopathic Product

Kanmet 40

Number 615

Homeopathic Product

Chamomilla 200C HPUS, Belladonna 30C HPUS

Helps improve tinnitus in the ear with vertigo

Quantity

96 Pills